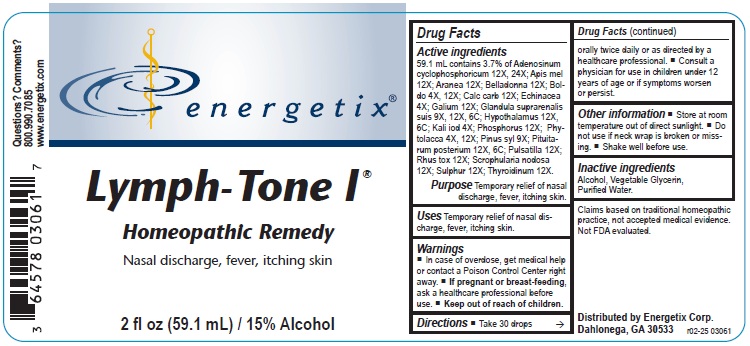 DRUG LABEL: Lymph-Tone
NDC: 64578-0179 | Form: LIQUID
Manufacturer: Energetix Corporation
Category: homeopathic | Type: HUMAN OTC DRUG LABEL
Date: 20250715

ACTIVE INGREDIENTS: ADENOSINE CYCLIC PHOSPHATE 12 [hp_X]/1 mL; APIS MELLIFERA 12 [hp_X]/1 mL; ARANEUS DIADEMATUS 12 [hp_X]/1 mL; ATROPA BELLADONNA 12 [hp_X]/1 mL; PEUMUS BOLDUS LEAF 4 [hp_X]/1 mL; OYSTER SHELL CALCIUM CARBONATE, CRUDE 12 [hp_X]/1 mL; ECHINACEA ANGUSTIFOLIA 4 [hp_X]/1 mL; GALIUM APARINE 12 [hp_X]/1 mL; SUS SCROFA ADRENAL GLAND 9 [hp_X]/1 mL; BOS TAURUS HYPOTHALAMUS 12 [hp_X]/1 mL; POTASSIUM IODIDE 4 [hp_X]/1 mL; PHOSPHORUS 12 [hp_X]/1 mL; PHYTOLACCA AMERICANA ROOT 4 [hp_X]/1 mL; PINUS SYLVESTRIS LEAFY TWIG 9 [hp_X]/1 mL; SUS SCROFA PITUITARY GLAND, POSTERIOR 12 [hp_X]/1 mL; PULSATILLA VULGARIS 12 [hp_X]/1 mL; TOXICODENDRON PUBESCENS LEAF 12 [hp_X]/1 mL; SCROPHULARIA NODOSA 12 [hp_X]/1 mL; SULFUR 12 [hp_X]/1 mL; THYROID, UNSPECIFIED 12 [hp_X]/1 mL
INACTIVE INGREDIENTS: WATER; ALCOHOL; GLYCERIN

Lymph-tone I

ACTIVE INGREDIENT

Active ingredients59.1 mL contains 3.7% of Adenosinum cyclophosphoricum 12X, 24X; Apismel 12X; Aranea 12X; Belladonna 12X; Boldo 4X, 12X; Calc carb 12X; Echinacea 4X; Galium 12X; Glandula suprarenalis suis 9X, 12X, 6C; Hypothalamus 12X, 6C; Kali iod 4X; Phosphorus 12X; Phytolacca 4X,12X; Pinus syl 9X; Pituitarum posterium 12X, 6C; Pulsatilla 12X; Rhus tox 12X; Scrophularia nodosa 12X; Sulphur 12X; Thyroidinum 12X.

Claims based on traditional homeopathic practice, not accepted medical evidence. Not FDA evaluated.

INDICATIONS AND USAGE

Uses Temporary relief of nasal discharge, fever, itching skin.

Warnings

- In case of overdose, get medical help or contact a Poison Control Center right away.
- If pregnant or breast-feeding, ask a healthcare professional before use.

- Keep out of reach of children.

Directions

- Take 30 drops orally twice daily or as directed by a healthcare professional.

- Consult a physician for use in children under 12 years of age or if symptoms worsen or persist.

Other information

- Take 30 drops orally twice daily or as directed by a healthcare professional.
- Consult a physician for use in children under 12 years of age or if symptoms worsen or persist.

Inactive Ingredients Alcohol, Vegetable Glycerin, Purified Water

QUESTIONS

Distributed by
Energetix Corp.
Dahlonega, GA 30533

Questions? Comments?

800.990.7085
www.energetix.com

PACKAGE LABEL

energetix

Lymph-Tone I

Homeopathic Remedy

Nasal discharge, fever, itching skin.
2 fl oz (59.1 mL) / 15% Alcohol

PURPOSE

Purpose Temporary relief of Nasal discharge, fever, Itching skin.